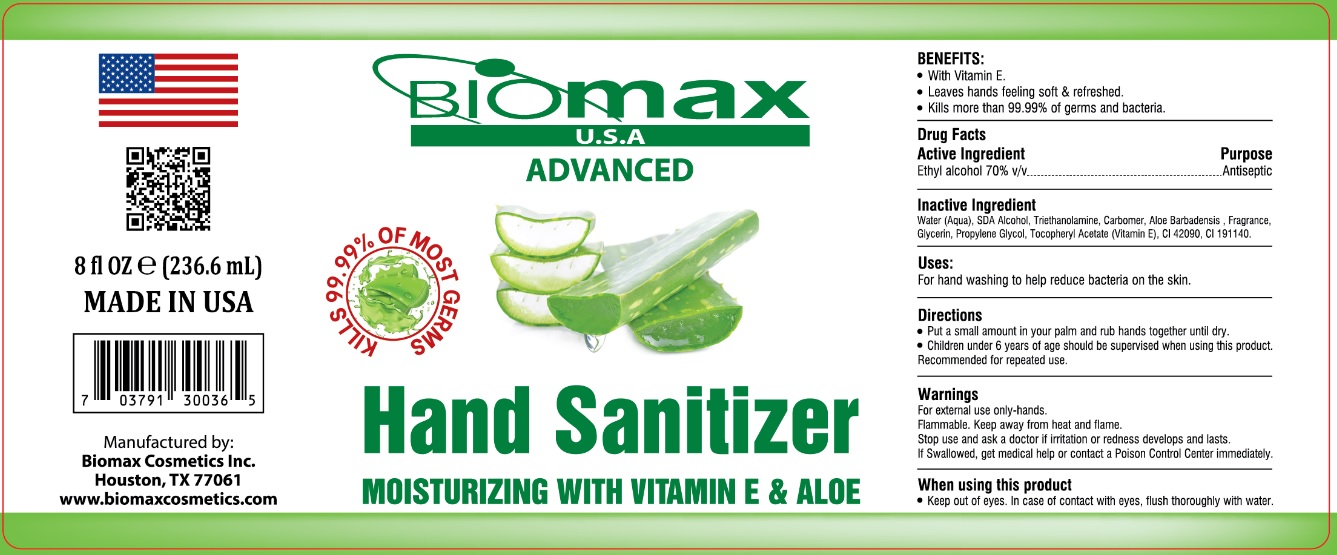 DRUG LABEL: Biomax USA HAND SANITIZER
NDC: 77369-927 | Form: LIQUID
Manufacturer: Biomax Cosmetics
Category: otc | Type: HUMAN OTC DRUG LABEL
Date: 20200727

ACTIVE INGREDIENTS: ALCOHOL 70 mL/100 mL
INACTIVE INGREDIENTS: WATER; TROLAMINE; CARBOMER HOMOPOLYMER, UNSPECIFIED TYPE; ALOE; GLYCERIN; PROPYLENE GLYCOL; .ALPHA.-TOCOPHEROL ACETATE; FD&C BLUE NO. 1; FD&C YELLOW NO. 5

Biomax ADVANCED Hand Sanitizer

Active Ingredient

Ethyl alcohol 70% v/v

Purpose

Antiseptic

Inactive Ingredient

Water(Aqua), SDA Alcohol, Triethanolamine, Carbomer, Aloe Barbadensis, Fragrance, Glycerin, Propylene Glycol, Tocopheryl Acetate (Vitamin E), CI 42090, CI 19140.

Uses:

For hand washing to help reduce bacteria on the skin.

Directions

• Put a small amount in your palm and rub hands together until dry.

• Children under 6 years of age should be supervised when using this product. Recommended for repeated use.

Warnings

For external use only-hands.

Flammable. Keep away from heat and flame.

Stop use and ask a doctor if irritation or redness develops and lasts.

When using this product

• Keep out of eyes. In case of contact with eyes, flush thoroughly with water.

KEEP OUT OF REACH OF CHILDREN

If Swallowed, get medical help or contact a Poison Control Center immediately.

ADVANCED Hand Sanitizer

MOISTURIZING WITH VITAMIN E & ALOE

KILLS 99.99% OF MOST GERMS

MADE IN USA

Manufactured by:

Biomax Cosmetics Inc.

Houston, TX 77061

www.biomaxcosmetics.com

BENEFITS:

• With Vitamin E.

• Leaves hands feeling soft & refreshed.

• Kills more than 99.99% of germs and bacteria.